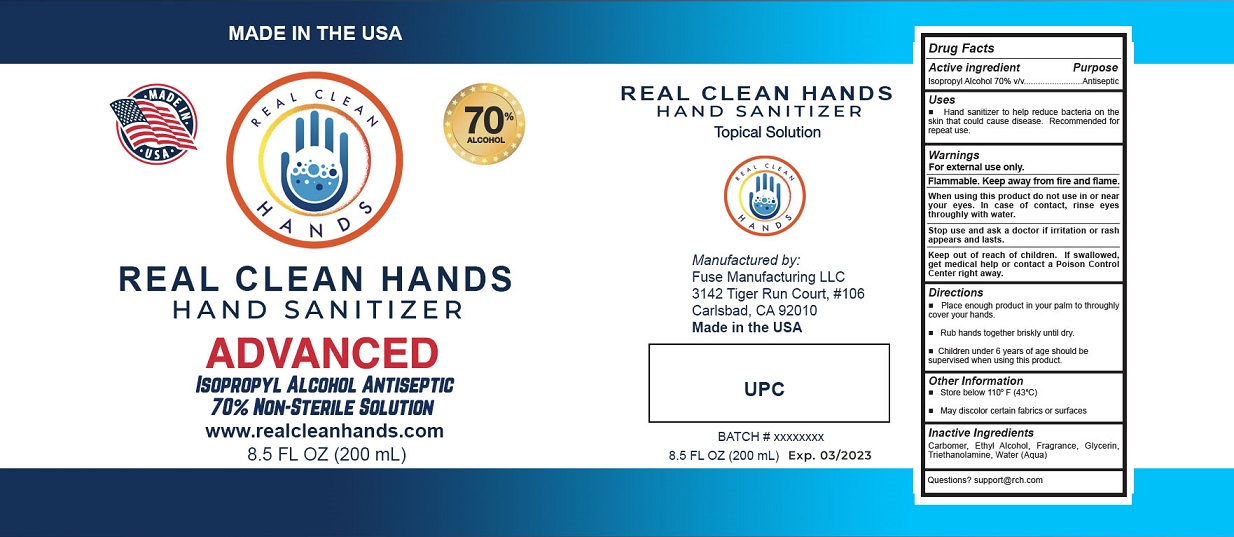 DRUG LABEL: Real clean hands
NDC: 79371-001 | Form: GEL
Manufacturer: FUSE MANUFACTURING LLC
Category: otc | Type: HUMAN OTC DRUG LABEL
Date: 20200703

ACTIVE INGREDIENTS: ISOPROPYL ALCOHOL 70 mL/100 mL
INACTIVE INGREDIENTS: CARBOMER HOMOPOLYMER, UNSPECIFIED TYPE; GLYCERIN; WATER; TROLAMINE; ALCOHOL

Active Ingredient

Isopropyl Alcohol 70% v/v.

Purpose

Antiseptic

Uses

Hand Sanitizer to help reduce bacteria that potentially can cause disease. Recommended for repeated use.

Warnings

For external use only. Flammable. Keep away from heat or flame.

When using this product keep out of eyes, ears, and mouth. In case of contact with eyes, rinse eyes thoroughly with water.
Stop use and ask a doctor if irritation or rash appears and lasts.

Keep out of reach of children. If swallowed, get medical help or contact a Poison Control Center right away.

Directions

- Place enough product in your palm to thoroughly cover your hands. Rub hands together briskly until dry.
- Children under 6 years of age should be supervised when using this product.

Other information

- Store below 110oF (43oC).
- May discolor certain fabrics or surfaces.

Inactive ingredients

Carbomer, ethyl alcohol, fragrance, glycerin, Triethanolamine, water (aqua)

Questions? support@rch.com